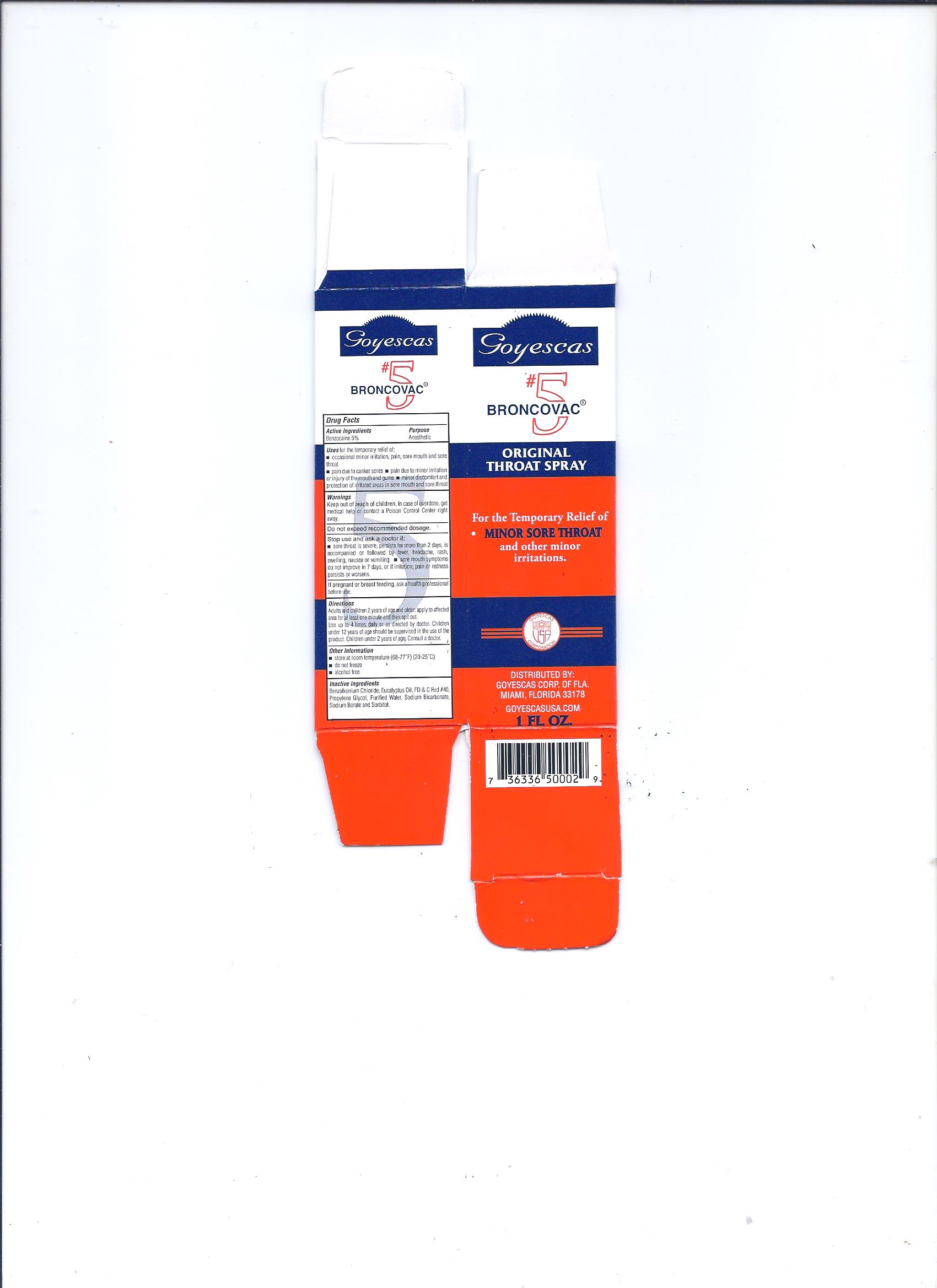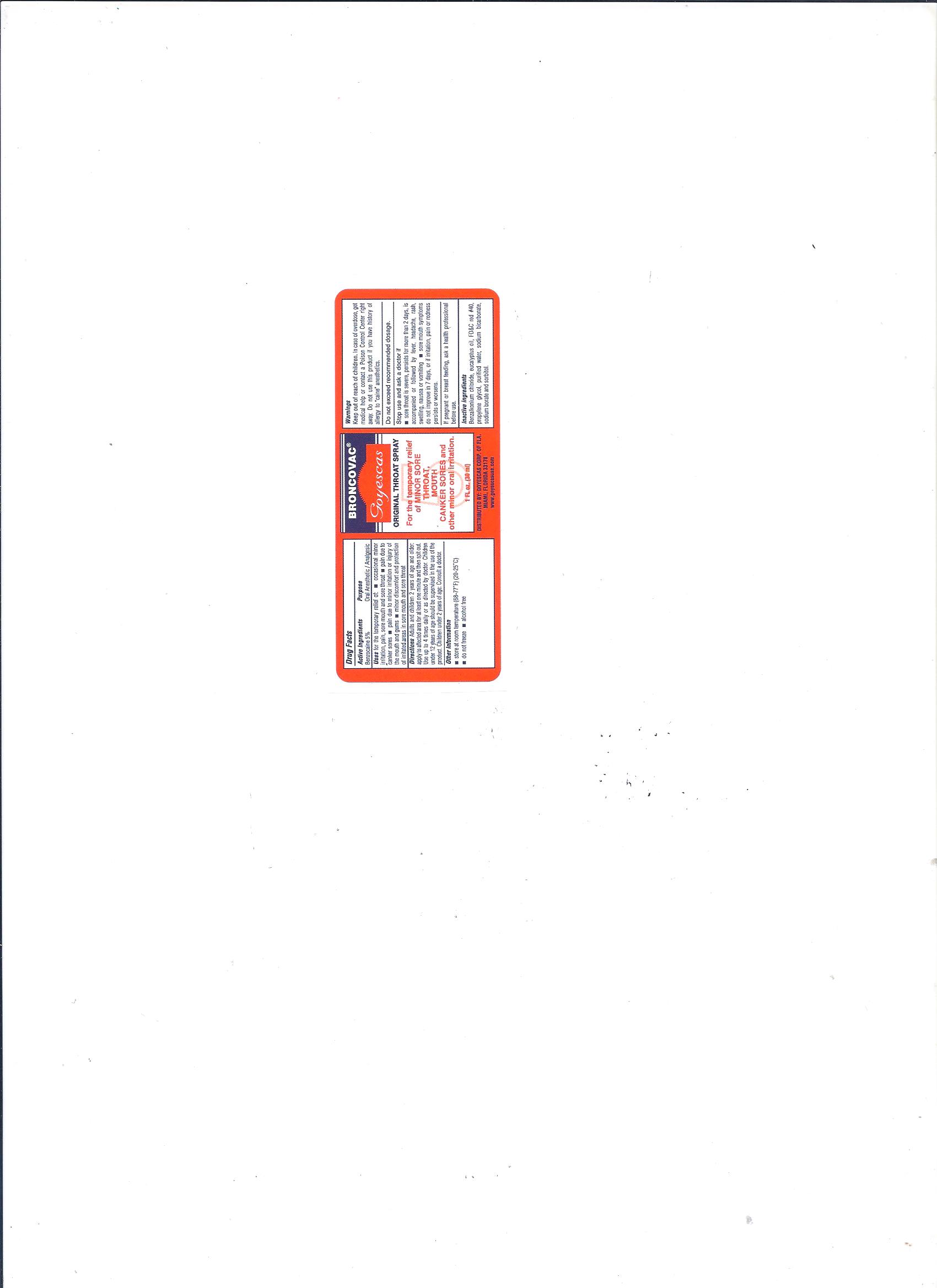 DRUG LABEL: Goyescas Broncovac 5
NDC: 11856-5002 | Form: LIQUID
Manufacturer: GOYESCAS OF FLA
Category: otc | Type: HUMAN OTC DRUG LABEL
Date: 20151019

ACTIVE INGREDIENTS: BENZOCAINE 50 mg/1 mL
INACTIVE INGREDIENTS: FD&C RED NO. 40; WATER; SODIUM BICARBONATE; SODIUM BORATE; SORBITOL; BENZALKONIUM CHLORIDE; EUCALYPTUS OIL

Dosage & Administration

Directions

Adults and children 2 years of age and older, apply to affected area for at least one minute and then spit out. Use up to 4 times daily or as directed by doctor. Children under 12 years of age should be supervised in the used of the product. Children 2 years of age: Consult a doctor.

Warnings

Keep away of reach from children. In case of overdose, get medical help or contact a Poison Control Center right away. Do not exceed recommended dosage. Stop use and ask a Doctor if: Sore throat is severe, persists for more than 2 days, is accompanied or followed by fever, headache, rash, swelling, nausea or vomiting, sore mouth symptoms do not improve in 7 days or if irritation, pain or redness persist or worsens. If pregnant or breast feeding, ask a health professional before use.

Inactive Ingredients

Benzalkonium chloride, Eucalyptus oil, FD&C Red #40, Propylene Glycol, Purified Water, Sodium Bicarbonate, Sodium Borate and sorbitol

Uses

Uses for the temporary relief of:

Occasional minor irritation, pain, sore mouth and throat. Pain due to canker sores. Pain due to minor irritation of injury of the mouth and gums, minor discomfort and protection of irritated area in sore mouth and sore throat.

Purpose

DRUG FACTS PURPOSE

Benzocaine 5% Anesthetic

Warnings

Keep away of reach from children. In case of overdose, get medical help or contact a Poison Control Center right away. Do not exceed recommended dosage. Stop use and ask a Doctor if: Sore throat is severe, persists for more than 2 days, is accompanied or followed by fever, headache, rash, swelling, nausea or vomiting, sore mouth symptoms do not improve in 7 days or if irritation, pain or redness persist or worsens. If pregnant or breast feeding, ask a health professional before use.

Active Ingredients

DRUG FACTS

ACTIVE INGREDIENTS PURPOSE

Benzocaine 5% Anesthetic

DRUG FACTS

ACTIVE INGREDIENTS PURPOSE

Benzocaine 5% Anesthetic

Uses for the temporary relief of:

Occasional minor irritation, pain, sore mouth and throat. Pain due to canker sores. Pain due to minor irritation of injury of the mouth and gums, minor discomfort and protection of irritated area in sore mouth and sore throat.

Warnings

Keep away of reach from children. In case of overdose, get medical help or contact a Poison Control Center right away. Do not exceed recommended dosage. Stop use and ask a Doctor if: Sore throat is severe, persists for more than 2 days, is accompanied or followed by fever, headache, rash, swelling, nausea or vomiting, sore mouth symptoms do not improve in 7 days or if irritation, pain or redness persist or worsens. If pregnant or breast feeding, ask a health professional before use.

Directions

Adults and children 2 years of age and older, apply to affected area for at least one minute and then spit out. Use up to 4 times daily or as directed by doctor. Children under 12 years of age should be supervised in the used of the product. Children 2 years of age: Consult a doctor.

Other Information

Store at room temperature (68-77F) (20-25C)

Do not freeze

Alcohol Free

Inactive ingredients

Benzalkonium chloride, Eucalyptus oil, FD&C Red #40, Propylene Glycol, Purified Water, Sodium Bicarbonate, Sodium Borate and sorbitol.